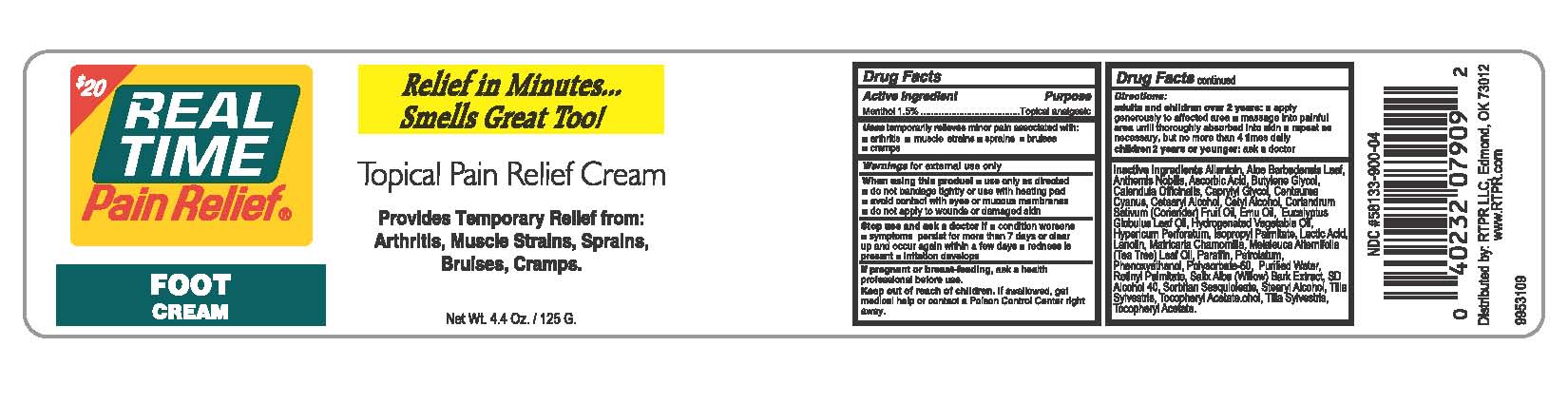 DRUG LABEL: Real Time Pain Relief Foot Cream
NDC: 58133-900 | Form: CREAM
Manufacturer: Cosmetic Specialty labs, Inc.
Category: otc | Type: HUMAN OTC DRUG LABEL
Date: 20180103

ACTIVE INGREDIENTS: MENTHOL 1.5 g/100 g
INACTIVE INGREDIENTS: TILIA X EUROPAEA FLOWER; ALPHA-TOCOPHERYLOXYACETIC ACID; ASCORBIC ACID; BUTYLENE GLYCOL; MATRICARIA CHAMOMILLA FLOWERING TOP OIL; POLYSORBATE 60; ALOE VERA LEAF; ALLANTOIN; CHAMOMILE FLOWER OIL; LACTIC ACID; CALENDULA OFFICINALIS FLOWER; LANOLIN; MELALEUCA ALTERNIFOLIA LEAF; CENTAUREA CYANUS FLOWER; CETYL ALCOHOL; CORIANDER OIL; POLYSORBATE 20; EMU OIL; WATER; SALIX ALBA BARK; PARAFFIN; PETROLATUM; CAPRYLYL GLYCOL; EUCALYPTUS GLOBULUS LEAF; HYDROGENATED COTTONSEED OIL; HYPERICUM PERFORATUM; PHENOXYETHANOL; RETINYL PROPIONATE; .ALPHA.-ISOBUTYLPHENETHYL ALCOHOL; SODIUM BORATE; SORBITAN SESQUIOLEATE; ISOSTEARYL ALCOHOL

Real Time Pain Relief Foot Cream

ACTIVE INGREDIENT

Menthol 1.5%

PURPOSE

Topical analgesic

KEEP OUT OF REACH OF CHILDREN

If swallowed, get medical help or contact a poison control center right away.

USES

Temporarily relieves minor pain associated with

- arthritis

- muscle strains
- sprains
- bruises
- cramps

WARNINGS

for external use only

When using this product

- use only as directed
- do not bandage tightly or use with heating pad
- avoid contact with eyes or mucus membranes
- do not apply to wounds or damaged skin

Stop using and ask a doctor if

- condition worsens
- symptoms persist for more than 7 days or clear up and occur again within a few days
- redness is present
- irritation develops

If pregnant or breast-feeding

ask a health professional before use

DIRECTIONS

adults and children over 2 years

- apply generously to affected area
- massage into painful area until throughly absorbed into skin
- repeat as necessary, but no more than 4 times daily

Children 2 years or younger:ask a doctor

INACTIVE INGREDIENTS

Allantoin, Aloe barbadensis Leaf Juice, Anthemis nobilis (Roman Chamomile), Ascorbic Acid, Butylene Glycol, Calendula officianlis (Marigold), Caprylyl Glycol, Centaurea cyanus (Cornflower), Cetearyl Alcohol, Cetyl Alcohol, Coriandrum sativum (Coriander) Fruit Oil, Emu Oil, Eucalyptus globulus Leaf Oil, Hydrogenated Vegetable Oil, Hypericum perforatum (St. John’s Wort), Lactic Acid, Lanolin, Matricaria chamomilla (Chamomile), Melaleuca alternifolia (Tea Tree) Leaf Oil, Paraffin, Petrolatum, Phenoxyethanol, Polysorbate-20, Polysorbate-60, Purified Water, Retinyl Palmitate, Salix alba (Willow) Bark Extract, SD Alcohol 40, Sodium Borate, Sorbitan Sesquioleate, Stearyl Alcohol, Tilia sylvestris (Lime Tree), Tocopheryl Acetate.